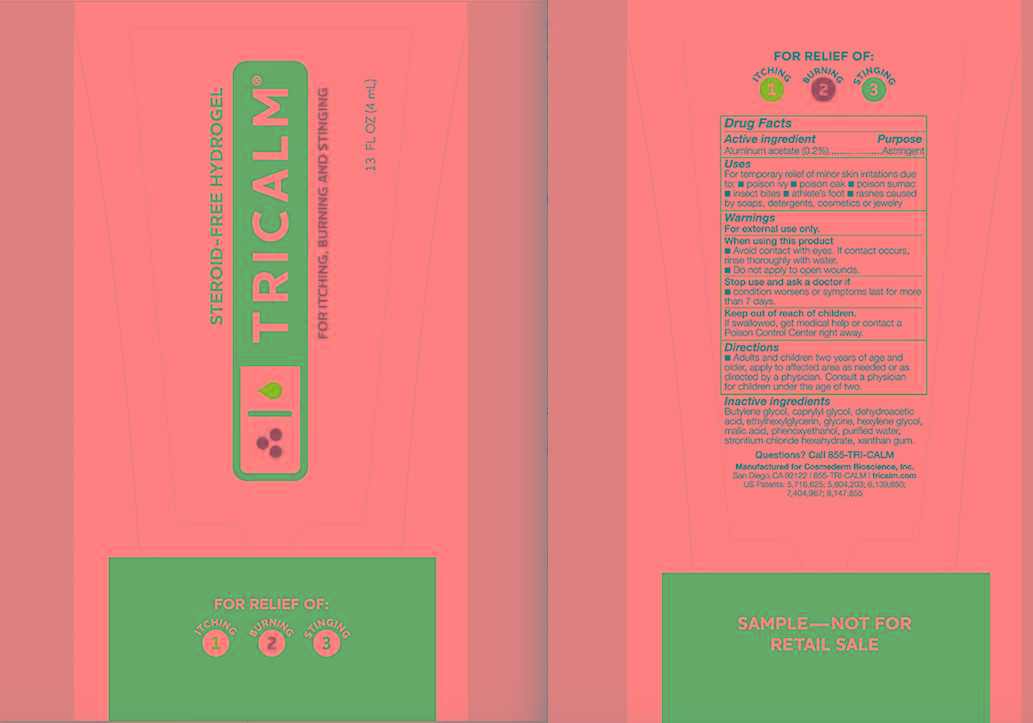 DRUG LABEL: Astringent
NDC: 35192-005 | Form: GEL
Manufacturer: CA-BOTANA INTERNATIONAL
Category: otc | Type: HUMAN OTC DRUG LABEL
Date: 20150101

ACTIVE INGREDIENTS: ALUMINUM ACETATE 0.008 mg/4 mL
INACTIVE INGREDIENTS: Butylene Glycol; Caprylyl Glycol; Dehydroacetic Acid; Ethylhexylglycerin; Glycine; Hexylene Glycol; Malic Acid; Phenoxyethanol; Water; Strontium Chloride Hexahydrate; Xanthan Gum

Hydrogel Formulated with COSMEDERM7 For temporary Relief of Minor Itching and Burning

WARNINGS

For external use only. Avoid contact with eyes. Keep out of reach of children. Do not apply to open wounds. STOP USE AND ask a doctor if condition worsens or symptoms persist for more than seven days, discontinue use of the product.

DOSAGE AND ADMINISTRATION

Adults and children two years of age and older, apply to affected area not more than three times daily or as directed by a doctor. Consult a physician for children under the age of two.

INACTIVE INGREDIENT

Butylene Glycol,
Caprylyl Glycol,
Dehydroacetic Acid,
Ethylhexylglycerin,
Glycine,
Hexylene Glycol,
Malic Acid,
Phenoxyethanol,
Purified Water,
Strontium Chloride Hexahydrate,
Xanthan Gum.

PURPOSE

Astringent

ACTIVE INGREDIENT

1. Aluminium acetate

KEEP OUT OF REACH OF CHILDREN

For external use only.
Avoid contact with eyes.
Keep out of reach of children.
Do not apply to open wounds.
STOP USE AND ask a doctor if condition worsens or
symptoms persist for more than seven days, discontinue
use of the product.

INDICATIONS AND USAGE

1. Adults and children two years of age and older, apply to affected area not more than three times daily or as directed by a doctor. Consult a physician for children under the age of two.